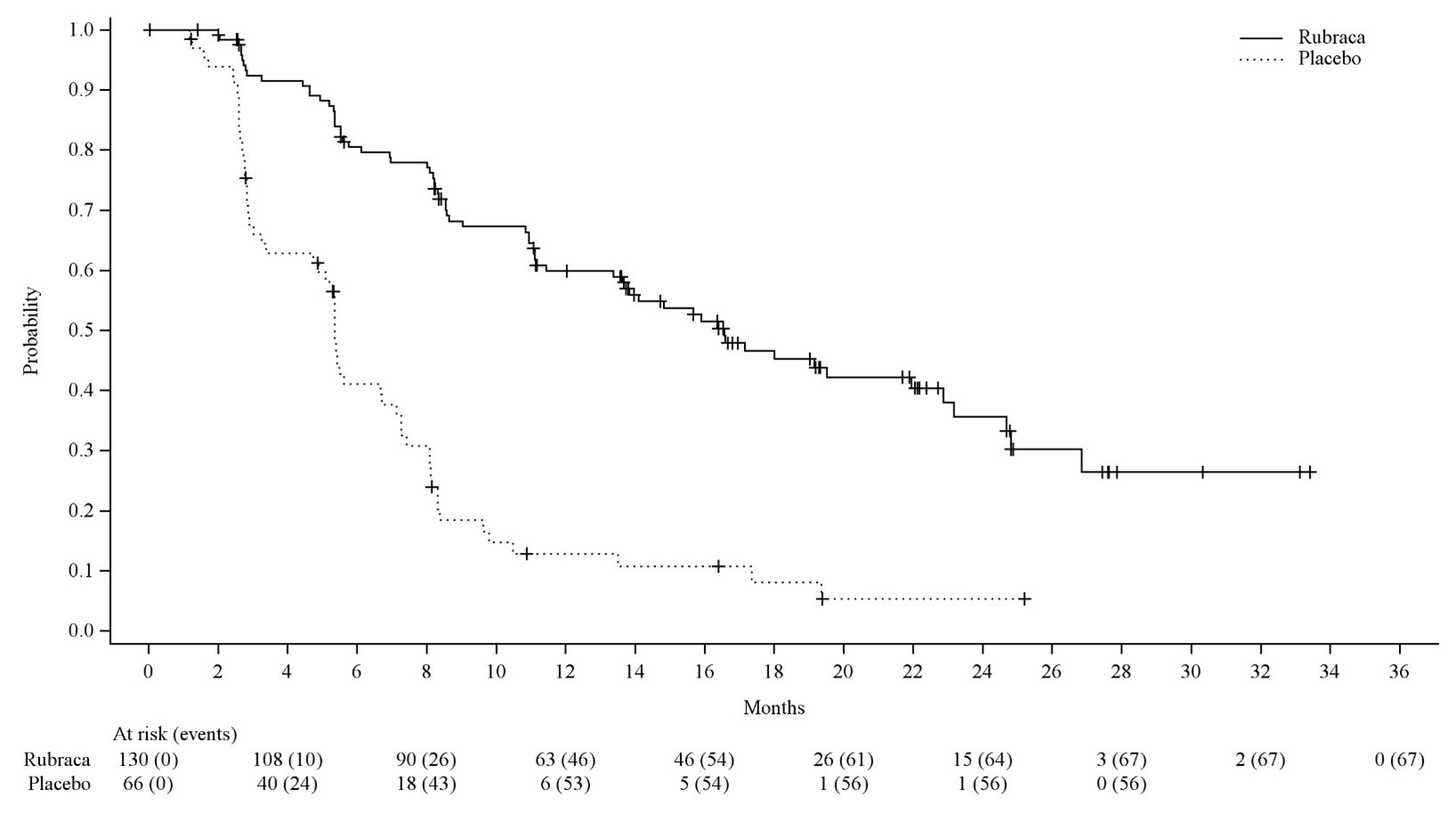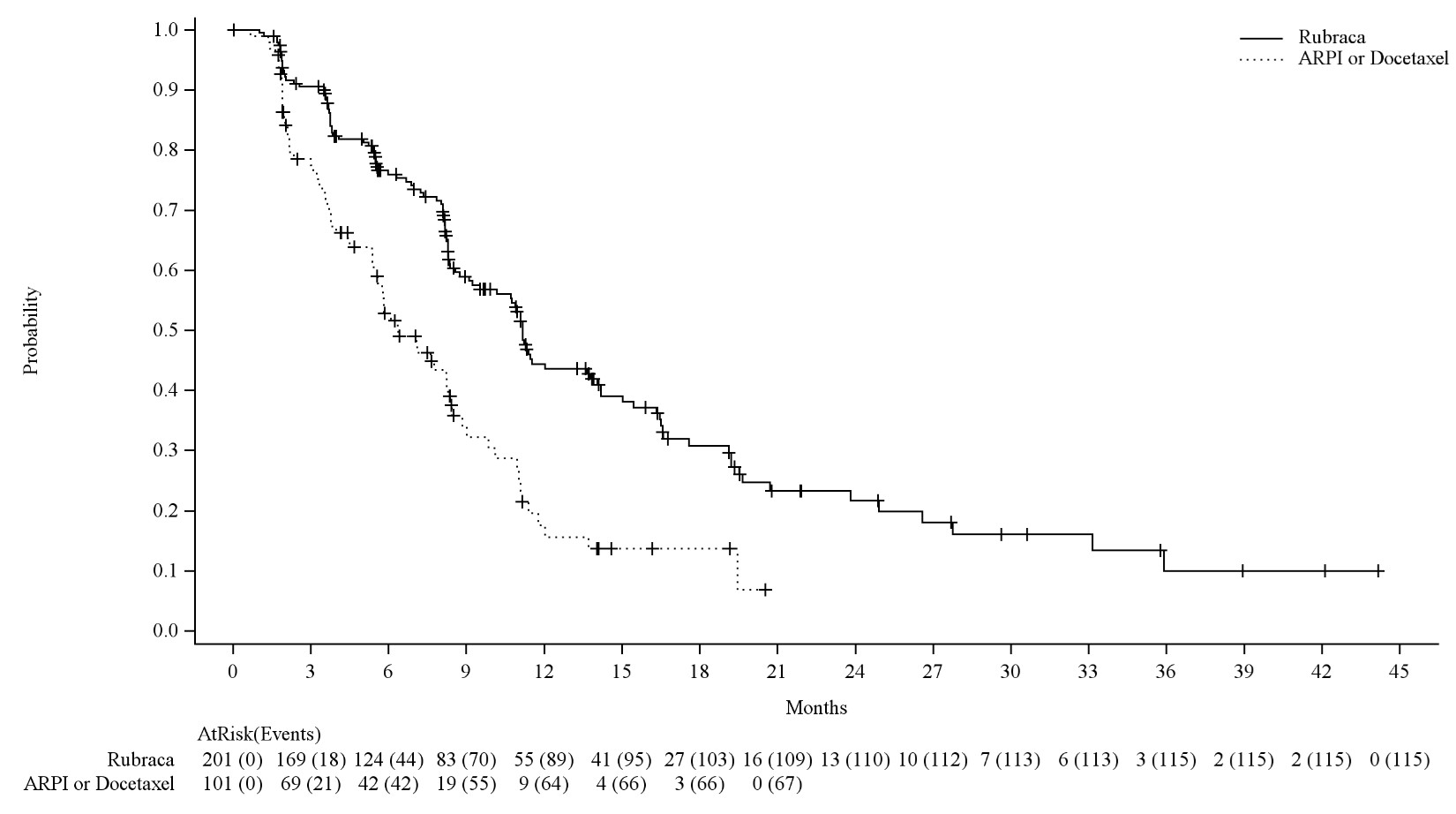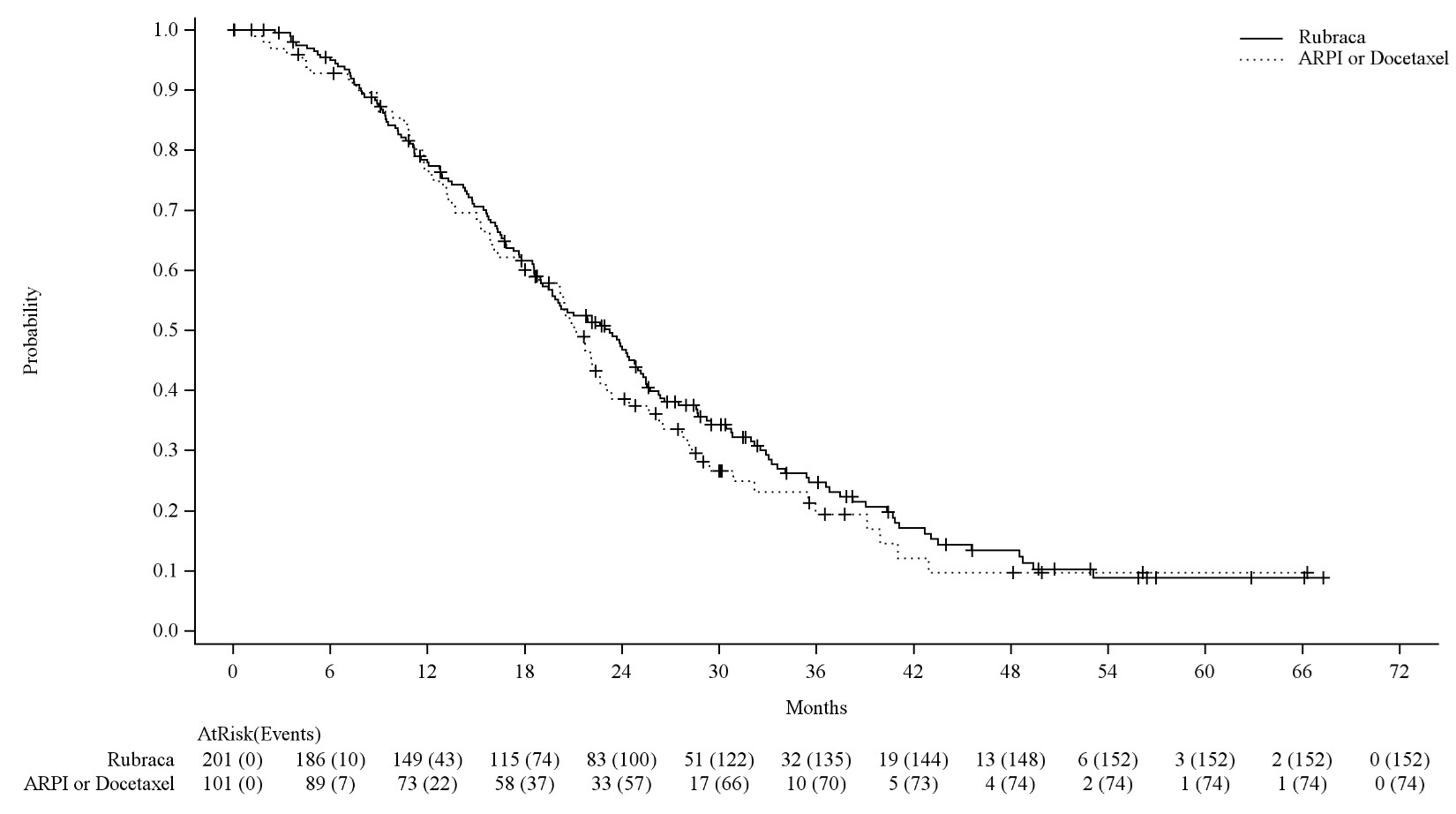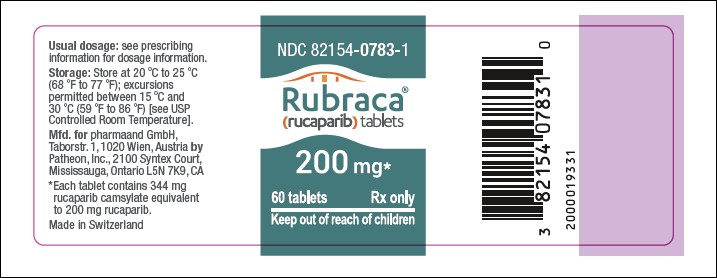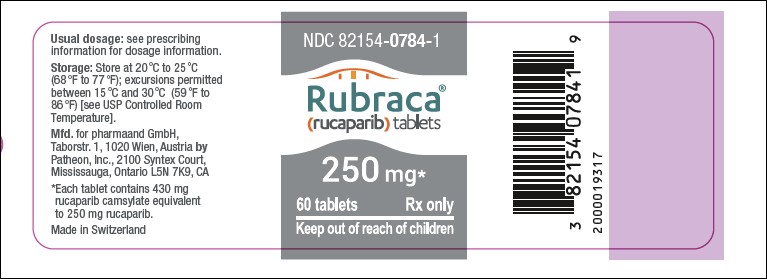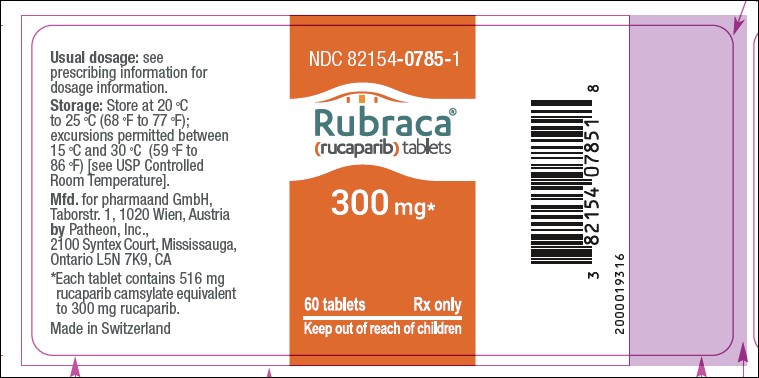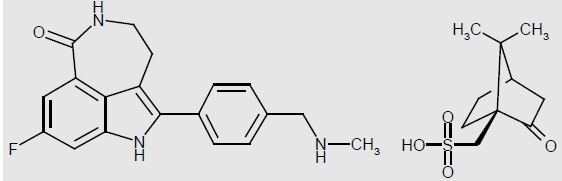 DRUG LABEL: Rubraca
NDC: 82154-0783 | Form: TABLET, FILM COATED
Manufacturer: pharmaand GmbH
Category: prescription | Type: HUMAN PRESCRIPTION DRUG LABEL
Date: 20251231

ACTIVE INGREDIENTS: RUCAPARIB CAMSYLATE 200 mg/1 1
INACTIVE INGREDIENTS: SODIUM STARCH GLYCOLATE TYPE A POTATO; SILICON DIOXIDE; MAGNESIUM STEARATE; POLYVINYL ALCOHOL, UNSPECIFIED; TITANIUM DIOXIDE; POLYETHYLENE GLYCOL, UNSPECIFIED; TALC; FD&C BLUE NO. 1; FD&C BLUE NO. 2; CELLULOSE, MICROCRYSTALLINE

HIGHLIGHTS OF PRESCRIBING INFORMATION

These highlights do not include all the information needed to use RUBRACA safely and effectively. See full prescribing information for RUBRACA.
RUBRACA®(rucaparib) tablets, for oral use
Initial U.S. Approval: 2016

RECENT MAJOR CHANGES

Indications and Usage (1.2) | 12/2025
Warnings and Precautions (5.1) | 12/2025

1 INDICATIONS AND USAGE

RUBRACA is a poly (ADP-ribose) polymerase (PARP) inhibitor indicated:

Ovarian cancer

- for the maintenance treatment of adult patients with a deleterious BRCAmutation (germline and/or somatic)-associated recurrent epithelial ovarian, fallopian tube, or primary peritoneal cancer who are in a complete or partial response to platinum-based chemotherapy. (1.1)

Prostate cancer

- for the treatment of adult patients with a deleterious BRCAmutation (germline and/or somatic)-associated metastatic castration-resistant prostate cancer (mCRPC) who have been treated with androgen receptor-directed therapy. Select patients for therapy based on an FDA-approved companion diagnostic for RUBRACA. (1.2, 2.1)

2 DOSAGE AND ADMINISTRATION

- Recommended dose is 600 mg orally twice daily with or without food. (2.2)
- Continue treatment until disease progression or unacceptable toxicity. (2.2)
- For adverse reactions, consider interruption of treatment or dose reduction. (2.3)
- Patients receiving RUBRACA for mCRPC should also receive a gonadotropin-releasing hormone (GnRH) analog concurrently or should have had bilateral orchiectomy. (2.2)

3 DOSAGE FORMS AND STRENGTHS

Tablets: 200 mg, 250 mg, and 300 mg (3)

4 CONTRAINDICATIONS

None. (4)

5 WARNINGS AND PRECAUTIONS

- Myelodysplastic Syndrome/Acute Myeloid Leukemia (MDS/AML): MDS/AML occurred in patients exposed to RUBRACA, and some cases were fatal. Monitor patients for hematological toxicity at baseline and monthly thereafter. Interrupt or reduce the dose based on severity of reaction. Discontinue if MDS/AML is confirmed. (2.3, 5.1)
- Embryo-Fetal Toxicity: RUBRACA can cause fetal harm. Advise of the potential risk to a fetus and to use effective contraception. (5.2, 8.1, 8.3)

6 ADVERSE REACTIONS

- Most common adverse reactions (≥10%) among patients with ovarian cancer were nausea, fatigue (including asthenia), anemia, ALT/AST increased, vomiting, diarrhea, decreased appetite, thrombocytopenia, dysgeusia, neutropenia, blood creatinine increased, dyspnea, dizziness, dyspepsia, photosensitivity reaction, and leukopenia. (6.1)
- Most common adverse reactions (≥10%) among patients with BRCA-mutated mCRPC were fatigue/asthenia, musculoskeletal pain, nausea, anemia, decreased appetite, increased ALT/AST, constipation, diarrhea, vomiting, thrombocytopenia, dyspnea, increased blood creatinine, edema, dizziness, weight decreased, abdominal pain, dysgeusia, rash, neuropathy peripheral, urinary tract infection, cough, headache, hemorrhage, neutropenia, and photosensitivity reaction. (6.1)

To report SUSPECTED ADVERSE REACTIONS, contact pharmaand agent at 1-800-506-8501 or FDA at 1-800-FDA-1088 orwww.fda.gov/medwatch.

8 USE IN SPECIFIC POPULATIONS

- Lactation: Advise women not to breastfeed. (8.2)

FULL PRESCRIBING INFORMATION

1 INDICATIONS AND USAGE

1.1 Maintenance Treatment of BRCA-mutated Recurrent Ovarian Cancer

RUBRACA is indicated for the maintenance treatment of adult patients with a deleterious BRCAmutation (germline and/or somatic)-associated recurrent epithelial ovarian, fallopian tube, or primary peritoneal cancer who are in a complete or partial response to platinum-based chemotherapy.

1.2 BRCA-mutated Metastatic Castration-Resistant Prostate Cancer

RUBRACA is indicated for the treatment of adult patients with a deleterious BRCAmutation (germline and/or somatic)-associated metastatic castration-resistant prostate cancer (mCRPC) who have been treated with androgen receptor-directed therapy. Select patients for therapy based on an FDA-approved companion diagnostic for RUBRACA [see Dosage and Administration(2.1)].

2 DOSAGE AND ADMINISTRATION

2.1 Patient Selection

Maintenance Treatment of BRCA-mutated Recurrent Ovarian Cancer

Select patients for the maintenance treatment of recurrent ovarian cancer with RUBRACA based on the presence of a deleterious BRCA mutation (germline and/or somatic) [see Clinical Studies (14.1)].

An FDA-approved test for the detection of deleterious germline and/or somatic BRCA mutations is not currently available.

Treatment of BRCA -mutated mCRPC after Androgen Receptor-directed Therapy

Select patients for the treatment of mCRPC with RUBRACA based on the presence of a deleterious BRCA mutation (germline and/or somatic) in plasma specimens [see Clinical Studies (14.2)]. A negative result from a plasma specimen does not mean that the patient’s tumor is negative for BRCA mutations. Should the plasma specimen have a negative result, consider performing further genomic testing using tumor specimens as clinically indicated.

Information on the FDA-approved tests for the detection of a BRCA mutation in patients with ovarian cancer or with prostate cancer is available at: http://www.fda.gov/CompanionDiagnostics.

2.2 Recommended Dose

The recommended dose of Rubraca is 600 mg (two 300 mg tablets) taken orally twice daily with or without food, for a total daily dose of 1,200 mg. (2.2)

Continue treatment until disease progression or unacceptable toxicity. (2.2)

For adverse reactions, consider interruption of treatment or dose reduction. (2.3)

Patients receiving RUBRACA for mCRPC should also receive a gonadotropin-releasing hormone (GnRH) analog concurrently or should have had bilateral orchiectomy. (2.2)

2.3 Dose Modifications for Adverse Reactions

To manage adverse reactions, consider interruption of treatment or dose reduction. Recommended Rubraca dose modifications for adverse reactions are indicated in Table 1.

Table 1. Recommended Dose Modifications for Adverse Reactions
Dose Reduction | Dose
Starting Dose | 600 mg twice daily (two 300 mg tablets)
First Dose Reduction | 500 mg twice daily (two 250 mg tablets)
Second Dose Reduction | 400 mg twice daily (two 200 mg tablets)
Third Dose Reduction | 300 mg twice daily (one 300 mg tablet)

3 DOSAGE FORMS AND STRENGTHS

- Tablets (200 mg): blue, round, immediate-release, film-coated, debossed with “C2”.
- Tablets (250 mg): white, diamond, immediate-release, film-coated, debossed with “C25”.
- Tablets (300 mg): yellow, oval, immediate-release, film-coated, debossed with “C3”.

4 CONTRAINDICATIONS

None.

5 WARNINGS AND PRECAUTIONS

5.1 Myelodysplastic Syndrome/Acute Myeloid Leukemia

Myelodysplastic Syndrome (MDS)/Acute Myeloid Leukemia (AML) occur in patients treated with RUBRACA, and are potentially fatal adverse reactions. In 2141 treated patients with ovarian and prostate cancer [see Adverse Reactions(6.1)], MDS/AML occurred in 34 patients (1.6%), including those in long term follow-up. Of these, 14 occurred during treatment or during the 28-day safety follow-up (0.7%). The duration of RUBRACA treatment prior to the diagnosis of MDS/AML ranged from < 2 months to approximately 72 months. The cases were typical of secondary MDS/cancer therapy-related AML; in all cases, patients had received previous platinum-containing chemotherapy regimens and/or other DNA damaging agents.

In ARIEL3, of patients with a germline and/or somatic BRCAmutation treated with RUBRACA, MDS/AML occurred in 9 out of 129 (7%) patients treated with RUBRACA and 4 out of 66 (6%) patients treated with placebo. The duration of therapy with RUBRACA in patients who developed secondary MDS/cancer therapy-related AML varied from 1.2 to 4.7 years.

In TRITON3, MDS/AML occurred in 2 out of 201 patients (1%) with a BRCAmutation treated with RUBRACA. The duration of therapy with RUBRACA in patients who developed secondary MDS/cancer therapy-related AML varied from 1.4 to 2.3 years.

Do not start Rubraca until patients have recovered from hematological toxicity caused by previous chemotherapy (≤ Grade 1). Monitor complete blood counts for cytopenia at baseline and monthly thereafter for clinically significant changes during treatment. For prolonged hematological toxicities (> 4 weeks), interrupt Rubraca or reduce dose according to Table 1 [see Dosage and Administration (2.3)] and monitor blood counts weekly until recovery. If the levels have not recovered to Grade 1 or less after 4 weeks or if MDS/AML is suspected, refer the patient to a hematologist for further investigations, including bone marrow analysis and blood sample for cytogenetics. If MDS/AML is confirmed, discontinue Rubraca.

5.2 Embryo-Fetal Toxicity

Rubraca can cause fetal harm when administered to a pregnant woman based on its mechanism of action and findings from animal studies. In an animal reproduction study, administration of rucaparib to pregnant rats during the period of organogenesis resulted in embryo-fetal death at exposures that were 0.04 times the AUC0-24hin patients receiving the recommended human dose of 600 mg twice daily. Apprise pregnant women of the potential risk to a fetus. Advise females of reproductive potential to use effective contraception during treatment and for 6 months following the last dose of Rubraca [see Use in Specific Populations (8.1, 8.3) and Clinical Pharmacology (12.1)].

Based on findings from genetic toxicity and animal reproduction studies, advise male patients with female partners of reproductive potential or who are pregnant to use effective contraception during treatment and for 3 months following the last dose of Rubraca [see Use in Specific Populations (8.1, 8.3)].

6 ADVERSE REACTIONS

The following serious adverse reactions are discussed elsewhere in the labeling:

- Myelodysplastic Syndrome/Acute Myeloid Leukemia [see Warnings and Precautions (5.1)].

6.1 Clinical Trials Experience

Because clinical trials are conducted under widely varying conditions, adverse reaction rates observed in the clinical trials of a drug cannot be directly compared to rates in the clinical trials of another drug and may not reflect the rates observed in practice.

The pooled safety population for patients with ovarian and prostate cancer in the WARNINGS AND PRECAUTIONS section reflect exposure to RUBRACA at 600 mg orally twice daily in 2141 patients treated on clinical trials including ARIEL3, TRITON2, and TRITON3. In ARIEL3 among the patients who received RUBRACA, 57% of patients were exposed for 6 months or longer and 33% were exposed for greater than one year. In TRITON3 among the patients with BRCA-mutated mCRPC who received RUBRACA, 66% were exposed for 6 months or longer and 34% were exposed for greater than one year.

In the pooled safety population for patients with ovarian cancer, the most common adverse reactions in ≥ 10% of patients were nausea (68%), asthenia/fatigue (65%), anemia/hemoglobin decreased (45%), AST/ALT increased (39%), vomiting (36%), diarrhea (29%), decreased appetite (27%), thrombocytopenia/platelet count decreased (25%), dysgeusia (24%), neutropenia/neutrophil count decreased (21%), blood creatinine increased (17%), dyspnea (16%), dizziness (14%), dyspepsia (11%), photosensitivity reaction (10%), and leukopenia/white blood cell count decreased (10%).

In the pooled safety population for patients with BRCA-mutated mCRPC (N=373) from TRITON2 and TRITON3, the most common adverse reactions in ≥ 10% of patients were fatigue/asthenia (61%), musculoskeletal pain (52%), nausea (52%), anemia/decreased hemoglobin (49%), decreased appetite (35%), increased ALT/AST (31%), constipation (30%), diarrhea (27%), vomiting (26%), thrombocytopenia/decreased platelet count (21%), dyspnea (20%), increased blood creatinine (19%), edema (19%), dizziness (19%), weight decreased (16%), abdominal pain (15%), dysgeusia (15%), rash (13%), neuropathy peripheral (13%), urinary tract infection (13%), cough (12%), headache (12%), hemorrhage (12%), neutropenia/decreased neutrophil count (12%), and photosensitivity reaction (10%).

CLINICAL TRIALS EXPERIENCE

Maintenance Treatment of BRCA-mutated Recurrent Ovarian Cancer

The safety of RUBRACA for the maintenance treatment of patients with BRCA-mutated recurrent epithelial ovarian, fallopian tube, or primary peritoneal cancer was investigated in ARIEL3, a randomized (2:1), double-blind, placebo-controlled study in which 195 patients with a deleterious BRC Amutation received either RUBRACA 600 mg orally twice daily (n=129) or placebo (n=66) until disease progression or unacceptable toxicity. The median duration of study treatment was 13.6 months (range: < 1 month to 39 months) for patients who received RUBRACA and 5.5 months for patients who received placebo.

Dose interruptions due to an adverse reaction of any grade occurred in 67% of patients receiving RUBRACA and 14% of those receiving placebo; dose reductions due to an adverse reaction occurred in 57% of RUBRACA patients and 6% of placebo patients. The most frequent adverse reactions leading to dose interruption or dose reduction of RUBRACA were thrombocytopenia (25%), anemia (19%), ALT/AST increased (16%), fatigue/asthenia (14%), and nausea (10%). Discontinuation due to adverse reactions occurred in 15% of RUBRACA patients and 5% of placebo patients. Specific adverse reactions that most frequently led to discontinuation in patients treated with RUBRACA were thrombocytopenia (4%), nausea (3%), and anemia (2%). Table 2 describes the adverse reactions occurring in ≥20% of patients; while Table 3 describes the laboratory abnormalities occurring in ≥25% of patients occurring in ARIEL3.

Table 2. Adverse Reactions in ≥ 20% of Patients with BRCA-mutated Ovarian Cancer in ARIEL3
Adverse reactions | RUBRACA N=129 |  | Placebo N=66
Adverse reactions | Grades 1-4 a % | Grades 3-4 % | Grades 1-4 a % | Grades 3-4 %
Gastrointestinal Disorders
Nausea | 79 | 2 | 29 | 0
Abdominal pain/distentionb | 48 | 3 | 49 | 2
Constipation | 39 | 4 | 36 | 2
Vomiting | 37 | 4 | 14 | 0
Diarrhea | 34 | 2 | 18 | 0
Stomatitisb | 28 | 0.8 | 12 | 0
General Disorders and Administration Site Conditions
Fatigue/asthenia | 74 | 9 | 52 | 5
Skin and Subcutaneous Tissue Disorders
Rashb | 45 | 0 | 23 | 0
Nervous System Disorders
Dysgeusia | 33 | 0 | 6 | 0
Headache | 22 | 0 | 15 | 2
Investigations
ALT/AST elevation | 33 | 16 | 3 | 0
Blood and Lymphatic System Disorders
Anemia | 41 | 26 | 6 | 0
Thrombocytopenia | 35 | 6 | 3 | 0
Neutropenia | 22 | 8 | 6 | 0
Respiratory, Thoracic, and Mediastinal Disorders
Nasopharyngitis/Upper respiratory tract infectionb | 29 | 0 | 20 | 2
Metabolism and Nutrition Disorders
Decreased appetite | 23 | 2 | 14 | 0
aNational Cancer Institute Common Terminology Criteria for Adverse Events (NCI CTCAE version 4.03)
bConsists of grouped related terms that reflect the medical concept of the adverse reaction

Adverse reactions occurring < 20% of patients treated with RUBRACA include insomnia (19%), dyspnea (17%), dizziness (15%), pyrexia (15%), dyspepsia (12%), peripheral edema (12%), and depression (11%).

Table 3. Laboratory Abnormalities in ≥ 25% of Patients with BRCA-mutated Ovarian Cancer in ARIEL3

Laboratory Parametera | RUBRACA N=129 |  | Placebo N=66
Laboratory Parametera | Grades 1-4 b % | Grades 3-4 % | Grades 1-4 b % | Grades 3-4 %
Chemistry
Increase in creatinine | 96 | 0 | 89 | 0
Increase in ALT | 67 | 11 | 6 | 0
Increase in AST | 59 | 1 | 6 | 0
Increase in cholesterol | 39 | 3 | 20 | 0
Increase in Alkaline Phosphatase | 39 | 0 | 3 | 0
Hematology
Decrease in hemoglobin | 61 | 18 | 14 | 2
Decrease in platelets | 47 | 2 | 8 | 0
Decrease in leukocytes | 39 | 3 | 23 | 0
Decrease in neutrophils | 38 | 6 | 18 | 2
Decrease in lymphocytes | 33 | 7 | 14 | 2
aPatients were allowed to enter clinical studies with laboratory values of CTCAE Grade 1.
bNCI CTCAE version 4.03.

CLINICAL TRIALS EXPERIENCE

Treatment of BRCA-mutated mCRPC after Androgen Receptor-directed Therapy

TRITON3

The safety of RUBRACA monotherapy was evaluated in patients with BRCA-mutated mCRPC who had progressed following prior treatment with androgen receptor-directed therapy and who had not received treatment with taxane-based chemotherapy in the castration-resistant setting. [see Clinical Studies(14.2)]. TRITON3 was a randomized, open-label, multi-center study, in which 298 patients with a deleterious BRCAmutation received either RUBRACA 600 mg twice daily (n=201) or physicians choice (n=97) of abiraterone acetate or enzalutamide, or docetaxel until disease progression, unacceptable toxicity, or up to 10 cycles for docetaxel. Among the patients who received RUBRACA, 66% were exposed for 6 months or longer and 34% were exposed for greater than one year.

Serious adverse reactions occurred in 27% of patients receiving RUBRACA. Serious adverse reactions in ≥2% of patients included anemia (4%), pneumonia (4%), urinary tract infection (3%), acute kidney injury (3%), myocardial ischemia/infarction (2%), and pulmonary embolism (2%). Fatal adverse reactions occurred in 1.5% of patients treated with RUBRACA, including cardiac failure, myocardial ischemia, and sepsis (1 patient each).

Permanent discontinuation due to adverse reactions occurred in 14% of patients treated with RUBRACA. Adverse reactions which resulted in permanent discontinuation of RUBRACA in ≥2% of patients included anemia (6%), fatigue/asthenia (3%), thrombocytopenia/platelet count decreased (3%), and nausea (2%).

Dosage interruptions of RUBRACA due to adverse reactions occurred in 53% of patients. Adverse reactions which required dosage interruption in ≥5% of patients included anemia (24%), fatigue/asthenia (10%), nausea (8%), and increase in ALT (5%).

Dose reductions of RUBRACA due to an adverse reaction occurred in 36% of patients. Adverse reactions which required dose reduction in ≥5% of patients included anemia (16%) and fatigue/asthenia (8%).

The most common adverse reactions (≥10%) in patients who received RUBRACA were fatigue/asthenia, musculoskeletal pain, nausea, decreased appetite, diarrhea, constipation, vomiting, dyspnea, dysgeusia, edema, abdominal pain, dizziness, weight decreased, rash, headache, peripheral neuropathy, photosensitivity reaction, and urinary tract infection.

The most common select laboratory abnormalities (≥25%) that worsened from baseline in patients who received RUBRACA were increased ALT, decreased neutrophils, decreased phosphate, decreased hemoglobin, increased AST, increased creatinine, increased glucose, decreased lymphocytes, decreased sodium, decreased platelets, increased calcium.

Tables 4 and 5 summarize the adverse reactions and laboratory abnormalities, respectively, in patients with BRCA-mutated mCRPC in TRITON3.

Table 4. Adverse Reactions in ≥ 10% of Patients with BRCA-mutated mCRPC in TRITON3
Adverse Reaction | RUBRACA N=201 |  | ARPI or Docetaxel N=97
Adverse Reaction | Grades 1-4a (%) | Grades 3-4 (%) | Grades 1-4a (%) | Grades 3-4 (%)
General disorders and administration site conditions
Fatigue/Asthenia | 61 | 7 | 65 | 10
Edemab | 18 | 0 | 20 | 0
Musculoskeletal and connective tissue disorders
Musculoskeletal painb | 53 | 7 | 57 | 8
Gastrointestinal disorders
Nausea | 51 | 2 | 22 | 1
Diarrhea | 31 | 2 | 29 | 1
Constipation | 31 | 2 | 17 | 1
Vomiting | 25 | 1 | 10 | 1
Abdominal painb | 17 | 1 | 10 | 1
Metabolism and nutrition disorders
Decreased appetite | 34 | 1 | 20 | 2
Respiratory, thoracic and mediastinal disorders
Dyspneab | 19 | 1 | 13 | 1
Nervous system disorders
Dysgeusiab | 18 | 0 | 12 | 0
Dizzinessb | 16 | 1 | 9 | 0
Headacheb | 12 | 0 | 9 | 0
Peripheral neuropathyb | 12 | 1 | 26 | 1
Investigations
Weight decreased | 16 | 1 | 13 | 0
Skin and subcutaneous tissue disorders
Rashb | 13 | 1 | 6 | 0
Photosensitivity reactionb | 12 | 1 | 0 | 0
Infections and infestations
Urinary tract infectionb | 10 | 3 | 4 | 1
a National Cancer Institute Common Terminology Criteria for Adverse Events (NCI CTCAE version 5.0)
b Includes multiple related terms

Clinically relevant adverse reactions occurring in <10% of patients treated with RUBRACA include cough, hemorrhage, fall, hypertension, dyspepsia, pruritus, pyrexia, stomatitis, venous thromboembolism, arrhythmia, hypersensitivity, and febrile neutropenia.

Table 5. Laboratory Abnormalities in ≥ 25% of Patients with BRCA-mutated mCRPC in TRITON3
Laboratory Parameter | Rubraca N=201a |  | ARPI or Docetaxel N=97a
Laboratory Parameter | Grades 1-4b (%) | Grades 3-4 (%) | Grades 1-4b (%) | Grades 3-4 (%)
Chemistry
Increase in ALT | 68 | 4 | 8 | 0
Decrease in phosphate | 64 | 8 | 45 | 5
Increase in AST | 59 | 2 | 7 | 0
Increase in creatinine | 56 | 1 | 16 | 0
Increase in glucose | 45 | 6 | 38 | 3
Decrease in sodium | 35 | 5 | 21 | 4
Increase in calcium | 29 | 3 | 19 | 2
Hematology
Decrease in neutrophils | 67 | 9 | 24 | 10
Decrease in hemoglobin | 60 | 23 | 31 | 2
Decrease in lymphocytes | 43 | 14 | 45 | 17
Decrease in platelets | 34 | 6 | 4 | 0
aDenominator for each laboratory parameter is based on the number of patients with a baseline and post-treatment laboratory value available for 192 to 201 patients in the RUBRACA Arm and 94 to 97 patients in the ARPI or Docetaxel Arm.
bNCI CTCAE version 5.0; decrease in phosphate is graded using NCI CTACE Version 4.03

TRITON2

The safety of RUBRACA 600 mg twice daily was evaluated in a single arm trial (TRITON2) [see Clinical Studies (14.2)]. TRITON2 enrolled 209 patients with HRR-mutated mCRPC, including 115 with BRCA-mutated mCRPC. Among the patients with BRCA-mutated mCRPC, the median duration of RUBRACA treatment was 6.5 months (range 0.5 to 26.7).

Fatal adverse reactions occurred in 1.7% of patients who received RUBRACA, including acute respiratory distress syndrome and pneumonia (1 patient each).

Permanent discontinuation of RUBRACA due to an adverse reaction occurred in 8% of patients.

Dosage interruption of RUBRACA due to an adverse reaction occurred in 57% of patients.

Dose reductions of RUBRACA occurred in 41% of patients.

Tables 6 and 7 summarize the adverse reactions and laboratory abnormalities, respectively, in patients with BRCA-mutated mCRPC in TRITON2.

Table 6. Adverse Reactions in ≥ 20% of Patients with BRCA-mutated mCRPC in TRITON2
Adverse Reaction | Rubraca N = 115
Adverse Reaction | Grades 1-4a (%) | Grades 3-4 (%)
General disorders and administration site conditions
Asthenia/Fatigue | 62 | 9
Gastrointestinal disorders
Nausea | 52 | 3
Constipation | 27 | 1
Vomiting | 22 | 1
Diarrhea | 20 | 0
Blood and lymphatic system disorders
Anemia | 43 | 25
Thrombocytopeniab | 25 | 10
Metabolism and nutrition disorders
Decreased appetite | 28 | 2
Skin and subcutaneous tissue disorders
Rashc | 27 | 2
aNCI CTCAE version 4.03.
bIncludes platelet count decreased
cIncludes blister, blood blister, dermatitis, dermatitis contact, eczema, genital rash, palmar-plantar erythrodysaesthesia syndrome, photosensitivity reaction, psoriasis, rash, rash maculo-papular, rash pruritic, skin exfoliation, skin lesion, urticaria

Other clinically relevant adverse reactions that occurred in less than 20% of patients included dyspnea, dizziness, bleeding, urinary tract infection, dysgeusia, dyspepsia, hypersensitivity (including flushing, asthma, choking sensation, periorbital swelling, swelling face, and wheezing), pneumonia, sepsis, ischemic cardiovascular events, renal failure, venous thromboembolism, and stomatitis.

Table 7. Laboratory Abnormalities in ≥ 35% (Grades 1-4) and ≥ 2% (Grades 3-4) Worsening from Baseline in Patients with BRCA-mutated mCRPC in TRITON2
Laboratory Parameter | Rubraca N = 115a
Laboratory Parameter | Grades 1-4b (%) | Grades 3-4 (%)
Clinical Chemistry
Increase in ALTc | 69 | 5
Decrease in phosphate | 68 | 15
Increase in alkaline phosphatase | 44 | 2
Increase in creatinine | 43 | 2
Increase in triglycerides | 42 | 5
Decrease in sodium | 38 | 3
Hematologic
Decrease in leukocytes | 69 | 5
Decrease in absolute neutrophil count | 62 | 5
aDenominator for each laboratory parameter is based on the number of patients with a baseline and post-treatment laboratory value available for 111 to 115 patients.
bNCI CTCAE version 5.0; decrease in phosphate is graded using NCI CTACE Version 4.03
cGrade 3-4 ALT or AST elevation led to drug interruption in 4 patients, of which 1 had dose reduction upon rechallenge.

7 DRUG INTERACTIONS

7.1 Effect of Rubraca on Other Drugs

DRUG INTERACTIONS

Certain CYP1A2, CYP3A, CYP2C9, or CYP2C19 Substrates

Concomitant administration of Rubraca with CYP1A2, CYP3A, CYP2C9, or CYP2C19 substrates can increase the systemic exposure of these substrates [see Clinical Pharmacology (12.3)] , which may increase the frequency or severity of adverse reactions of these substrates. If concomitant administration is unavoidable between Rubraca and substrates of these enzymes where minimal concentration changes may lead to serious adverse reactions, decrease the substrate dosage in accordance with the approved prescribing information.

If concomitant administration with warfarin (a CYP2C9 substrate) cannot be avoided, consider increasing the frequency of international normalized ratio (INR) monitoring.

8 USE IN SPECIFIC POPULATIONS

8.1 Pregnancy

PREGNANCY

Risk Summary

Based on findings from animal studies and its mechanism of action, Rubraca can cause fetal harm when administered to pregnant women. There are no available data in pregnant women to inform the drug-associated risk. In an animal reproduction study, administration of rucaparib to pregnant rats during organogenesis resulted in embryo-fetal death at maternal exposures that were 0.04 times the AUC0-24hin patients receiving the recommended dose of 600 mg twice daily [see Data]. Apprise pregnant women of the potential risk to a fetus.

The background risk of major birth defects and miscarriage for the indicated population is unknown. In the U.S. general population, the estimated background risk of major birth defects and miscarriage in clinically recognized pregnancies is 2% to 4% and 15% to 20%, respectively.

ANIMAL PHARMACOLOGY AND OR TOXICOLOGY

Data

Animal Data

In a dose range-finding embryo-fetal development study, pregnant rats received oral doses of 50, 150, 500, or 1000 mg/kg/day of rucaparib during the period of organogenesis. Post-implantation loss (100% early resorptions) was observed in all animals at doses greater than or equal to 50 mg/kg/day (with maternal systemic exposures approximately 0.04 times the human exposure at the recommended dose based on AUC0-24h).

8.2 Lactation

LACTATION

Risk Summary

There is no information regarding the presence of rucaparib in human milk, or on its effects on milk production or the breast-fed child. Because of the potential for serious adverse reactions in breast-fed children from Rubraca, advise lactating women not to breastfeed during treatment with Rubraca and for 2 weeks following the last dose.

8.3 Females and Males of Reproductive Potential

Rubraca can cause fetal harm when administered to a pregnant woman [see Use in Specific Populations (8.1)] .

FEMALES AND MALES OF REPRODUCTIVE POTENTIAL

Pregnancy Testing

Pregnancy testing is recommended for females of reproductive potential prior to initiating Rubraca.

FEMALES AND MALES OF REPRODUCTIVE POTENTIAL

Contraception

Females

Advise females of reproductive potential to use effective contraception during treatment and for 6 months following the last dose of Rubraca [see Use in Specific Populations (8.1)] .

Males

Based on findings in genetic toxicity and animal reproduction studies, advise male patients with female partners of reproductive potential or who are pregnant to use effective methods of contraception during treatment and for 3 months following last dose of Rubraca. Advise male patients not to donate sperm during therapy and for 3 months following the last dose of Rubraca [see Use in Specific Populations (8.1) and Nonclinical Toxicology (13.1)].

8.4 Pediatric Use

The safety and effectiveness of Rubraca in pediatric patients have not been established.

8.5 Geriatric Use

Of the 937 patients with ovarian cancer who received Rubraca in clinical trials including ARIEL3, 41% were age 65 or older and 10% were 75 years or older. No major differences in safety were observed between younger and older patients with ovarian cancer.

Of the 209 patients with mCRPC who received Rubraca in TRITON2, 77% were age 65 or older and 33% were 75 years or older. No major differences in safety were observed between younger and older patients with mCRPC.

8.6 Renal Impairment

No dosage modification is recommended for patients with mild to moderate renal impairment (creatinine clearance [CLcr] between 30 and 89 mL/min, as estimated by the Cockcroft-Gault method) [see Clinical Pharmacology (12.3)]. Rubraca has not been studied in patients with CLcr < 30 mL/min or patients on dialysis.

8.7 Hepatic Impairment

No dosage modification is recommended for patients with mild to moderate hepatic impairment (total bilirubin ≤ 3 x upper limit of normal [ULN] or AST > ULN) [see Clinical Pharmacology (12.3)] . Rubraca has not been studied in patients with severe hepatic impairment (total bilirubin > 3 x ULN and any AST).

11 DESCRIPTION

Rucaparib is an inhibitor of the mammalian polyadenosine 5'-diphosphoribose polymerase (PARP) enzyme. The chemical name is 8-fluoro-2-{4-[(methylamino)methyl]phenyl}-1,3,4,5-tetrahydro-6H-azepino[5,4,3-cd]indol-6-one ((1S,4R)-7,7-dimethyl-2-oxobicyclo[2.2.1]hept-1-yl)methanesulfonic acid salt. The chemical formula of rucaparib camsylate is C19H18FN3O•C10H16O4S and the relative molecular mass is 555.67 Daltons.

The chemical structure of rucaparib camsylate is shown below:

Rucaparib camsylate is a white to pale yellow powder; formulated into a tablet for oral use. Rucaparib shows pH-independent low solubility of approximately 1 mg/mL across the physiological pH range.

Rubraca (rucaparib) tablets contain rucaparib camsylate as the active ingredient. Each 200 mg tablet contains 344 mg rucaparib camsylate equivalent to 200 mg rucaparib free base. Each 250 mg tablet contains 430 mg rucaparib camsylate equivalent to 250 mg rucaparib free base. Each 300 mg tablet contains 516 mg rucaparib camsylate equivalent to 300 mg rucaparib free base.

The inactive ingredients in Rubraca tablets include: microcrystalline cellulose, sodium starch glycolate, colloidal silicon dioxide, and magnesium stearate. The cosmetic blue film coating for 200 mg tablets, cosmetic white film coating for 250 mg tablets, and cosmetic yellow film coating for 300 mg tablets is Opadry II containing polyvinyl alcohol, titanium dioxide, polyethylene glycol/macrogol, and talc. The coating is colorized as blue using brilliant blue aluminum lake and indigo carmine aluminum lake, or yellow using yellow iron oxide.

12 CLINICAL PHARMACOLOGY

12.1 Mechanism of Action

Rucaparib is an inhibitor of poly (ADP-ribose) polymerase (PARP) enzymes, including PARP-1, PARP-2, and PARP-3, which play a role in DNA repair. In vitrostudies have shown that rucaparib-induced cytotoxicity may involve inhibition of PARP enzymatic activity and increased formation of PARP-DNA complexes resulting in DNA damage, apoptosis, and cancer cell death. Increased rucaparib-induced cytotoxicity and anti-tumor activity was observed in tumor cell lines with deficiencies in BRCA1/2and other DNA repair genes. Rucaparib has been shown to decrease tumor growth in mouse xenograft models of human cancer with or without deficiencies in BRCA.

12.2 Pharmacodynamics

The exposure-response relationship and time course of pharmacodynamic response for the safety and effectiveness of rucaparib has not fully been characterized.

Cardiac Electrophysiology

A positive concentration-QTc relationship was observed in patients who were administered continuous dosages of Rubraca ranging from 40 mg once daily (0.03 times the approved recommended dosage) to 840 mg twice daily (1.4 times the approved recommended dosage). The mean (90% confidence interval [CI]) QTcF increase from baseline at steady state of Rubraca 600 mg twice daily was 14.9 msec (11.1, 18.7 msec).

12.3 Pharmacokinetics

The AUC and Cmaxof rucaparib demonstrated linear pharmacokinetics over a dose range from 240 mg to 840 mg twice daily (0.4 times to 1.4 times the approved recommended dosage). The mean (coefficient of variation [CV]) steady-state rucaparib Cmaxis 1,940 ng/mL (54%) and AUC0-12his 16,900 h×ng/mL (54%) at the approved recommended dosage. The mean AUC accumulation ratio is 3.5 to 6.2 fold.

Absorption

The median Tmax(min, max) at the steady state is 1.9 hours (0, 5.98) at the approved recommended dosage. The mean (min, max) absolute bioavailability is 36% (30%, 45%).

Effect of Food

Following a high-fat meal (approximately 800-1000 calories, including approximately 250 calories from carbohydrates, approximately 500-600 calories from fat, approximately 150 calories from protein), the Cmaxwas increased by 20%, AUC0-24hwas increased by 38%, and the Tmaxwas delayed by 2.5 hours, as compared to fasted conditions [see Dosage and Administration (2.2)] .

Distribution

The mean apparent volume of distribution is 2300 L (21%).

Rucaparib is 70% bound to human plasma proteins in vitro. Rucaparib preferentially distributed to red blood cells with a blood-to-plasma concentration ratio of 1.8.

Elimination

The mean apparent total clearance at steady state is 44.2 L/h (45%) and the mean terminal elimination half-life is 26 (39%) hours.

Metabolism

In vitro, rucaparib is primarily metabolized by CYP2D6 and to a lesser extent by CYP1A2 and CYP3A4. In addition to CYP-based oxidation, rucaparib also undergoes N-demethylation, N-methylation, and glucuronidation.

Excretion

Following a single oral dose of radiolabeled rucaparib, unchanged rucaparib accounted for 64% of the radioactivity. Rucaparib accounted for 45% and 95% of radioactivity in urine and feces, respectively.

Specific Populations

Age (20 to 86 years), race (White, Black, and Asian), sex, body weight (41 to 171 kg), mild to moderate renal impairment (CLcr ≥ 30 mL/min), mild hepatic impairment (total bilirubin < ULN and AST > ULN or total bilirubin 1 to 1.5 x ULN and any AST), and CYP2D6 or CYP1A2 genotype polymorphisms did not have a clinically meaningful effect on the pharmacokinetics of rucaparib. The effect of severe renal impairment (CLcr 15 to 29 mL/min), end-stage renal disease (CLcr < 15 mL/min), or severe hepatic impairment (total bilirubin > 3 x ULN and any AST) has not been studied.

Hepatic Impairment

Moderate hepatic impairment (total bilirubin > 1.5 to 3 x ULN and any AST) increased rucaparib AUC by 45%, but had no effect on Cmaxcompared to patients with normal hepatic function.

Drug Interaction Studies

Clinical Studies and Model-Informed Approaches

Effect of Other Drugs on Rucaparib

Concomitant administration of Rubraca with a proton pump inhibitor had no clinically meaningful effect on steady-state concentrations of rucaparib.

Effect of Rucaparib on Other Drugs

Concomitant administration of Rubraca with rosuvastatin (BCRP substrate) had no clinically meaningful effect on the concentrations of rosuvastatin.

Coadministration of Rubraca with the following substrates increased the Cmaxof each coadministered substrate by ≤ 1.1-fold and increased the AUC of each substrate as follows:

- Caffeine (CYP1A2): by 2.6-fold
- Midazolam (CYP3A4): by 1.4-fold
- Warfarin (CYP2C9): by 1.5-fold
- Omeprazole (CYP2C19): by 1.6-fold
- Digoxin (P-glycoprotein): by 1.2-fold

Concomitant administration of Rubraca with an oral contraceptive containing ethinylestradiol and levonorgestrel (CYP3A substrates): increased ethinylestradiol AUC by 1.4-fold and levonorgestrel AUC by 1.6-fold, but did not have a clinically meaningful effect on their Cmax.

In Vitro Studies

Cytochrome P450 (CYP) Enzymes: Rucaparib inhibited CYP2C8 and CYP2D6 and induced CYP1A2.

UDP-glucuronosyltransferase (UGT) Enzymes: Rucaparib inhibited UGT1A1.

Transporter Systems: Rucaparib is a substrate of P-gp and BCRP. Rucaparib is not a substrate of OATP1B1, OATP1B3, OAT1, OAT3, or OCT2.

Rucaparib inhibited OATP1B1, OATP1B3, OAT1, OAT3, MATE1, MATE2-K, OCT1, OCT2, and MRP4. Rucaparib did not inhibit MRP2, MRP3, or BSEP.

13 NONCLINICAL TOXICOLOGY

13.1 Carcinogenesis, Mutagenesis, Impairment of Fertility

Carcinogenicity studies have not been conducted with rucaparib.

Rucaparib was clastogenic in an in vitrochromosomal aberration assay in cultured human lymphocytes. The clastogenic response in mitotically-stimulated cells was anticipated based on the mechanism of action of rucaparib and indicates potential genotoxicity in humans. Rucaparib was not mutagenic in a bacterial reverse mutation (Ames) test.

Fertility studies with rucaparib have not been conducted. In 3-month repeat-dose general toxicology studies, rucaparib had no effects on male and female reproductive organs at doses up to 100 mg/kg/day and 20 mg/kg/day in rats and dogs, respectively. These dose levels resulted in systemic exposures of approximately 0.3 and 0.09 times the human exposure (AUC0-24h), respectively, at the recommended dose.

14 CLINICAL STUDIES

14.1 Maintenance Treatment of BRCA-mutated Recurrent Ovarian Cancer

The efficacy of Rubraca was investigated in ARIEL3 (NCT01968213), a double-blind, multicenter clinical trial in which 564 patients with recurrent epithelial ovarian, fallopian tube, or primary peritoneal cancer who were in response to platinum-based chemotherapy were randomized (2:1) to receive Rubraca tablets 600 mg orally twice daily (n=375) or placebo (n=189). Treatment was continued until disease progression or unacceptable toxicity. All patients had achieved a response (complete or partial) to their most recent platinum-based chemotherapy. Randomization was stratified by best response to last platinum (complete or partial), time to progression following the penultimate platinum therapy (6 to ≤12 months and >12 months), and tumor biomarker status.

Tumor tissue samples were tested using a clinical trial assay (CTA) (N=564) and an investigational Foundation Medicine tissue test (n=518). Of the samples evaluated with both tests, tumor BRCA (t BRCA) mutant status was confirmed for 99% (177/178) of t BRCA-positive patients determined by the CTA. Blood samples for 94% (186/196) of the t BRCA patients were evaluated using a central blood germline BRCA test. Based on these results, 70% (130/186) of the t BRCA patients had a germline BRCA mutation and 30% (56/186) had a somatic BRCA mutation. The efficacy results are based on the t BRCA (germline or somatic) subgroup.

The major efficacy outcome was investigator-assessed progression-free survival (PFS) evaluated according to Response Evaluation Criteria in Solid Tumors (RECIST), version 1.1 (v1.1). Overall survival (OS) was an additional outcome measure.

Of the 564 enrolled patients, 196 patients (35%) had a t BRCA mutation. Among the patients who had a tBRCA mutation, the median age was 58 years (range: 42 to 81) for patients receiving Rubraca and 59 years (range: 36 to 84) for those on placebo; the majority were White (84%); and 100% had an ECOG performance status of 0 or 1. All patients had received at least two prior platinum-based chemotherapies (range: 2 to 5). A total of 33% of patients were in complete response (CR) to their most recent therapy. The progression-free interval to penultimate platinum was 6-12 months in 41% of patients and >12 months in 59%. Prior bevacizumab therapy was reported for 22% of patients who received Rubraca and 17% of patients who received placebo. Measurable disease was present at baseline in 32% of patients.

ARIEL3 demonstrated a statistically significant improvement in PFS for patients randomized to Rubraca as compared with placebo in patients who had a t BRCA mutation. Results from a blinded independent radiology review were consistent.

Efficacy results for patients with a t BRCA mutation are summarized in Table 8 and Figure 1.

Table 8. Efficacy Results in Patients with tBRCA-mutated Ovarian Cancer – ARIEL3 (Investigator Assessment)a
 | Rubraca N=130 | Placebo N=66
Progression Free Survival
Number of events, n (%) | 67 (52%) | 56 (85%)
Median in months (95% CI) | 16.6 (13.4-22.9) | 5.4 (3.4-6.7)
HR (95% CI) | 0.23 (0.16, 0.34)
p-value | < 0.0001
at BRCA includes all patients with a deleterious germline or somatic BRCA mutation, as determined by the CTA.

Figure 1 Kaplan-Meier Curves of Progression-Free Survival in ARIEL3 as Assessed by Investigator: t BRCAGroup

A final OS analysis was conducted after 130 events were observed. Exploratory OS results showed a HR of 0.83 (95% CI: 0.58, 1.19) in the t BRCAsubgroup with a median OS of 45.9 months (95% CI: 37.7, 59.6) for patients treated with Rubraca and 47.8 months (95% CI: 43.2, 55.8) for patients on placebo.

14.2 BRCA-mutated Metastatic Castration-Resistant Prostate Cancer

TRITON3

The efficacy of RUBRACA was evaluated in TRITON3 (NCT02975934), a randomized, open-label, multi-center trial that evaluated RUBRACA compared to an androgen receptor pathway inhibitor (ARPI; enzalutamide or abiraterone acetate) or docetaxel in patients with progressive BRCAor ATMmutated metastatic castrate-resistant prostate cancer (mCRPC). The trial enrolled 405 patients with mCRPC, of whom 302 had BRCAmutations. Patients were required to have progressed on treatment with one ARPI and could not have received prior chemotherapy in the castrate-resistant setting. Prior taxane chemotherapy for castration-sensitive disease was permitted. Patients were required to be surgically or medically castrated with a castrate level of serum testosterone at study entry. BRCA gene mutation status was determined prospectively testing tumor tissue or plasma using Foundation Medicine, Inc. assays or through local testing.

Patients were randomized (2:1) to receive RUBRACA 600 mg twice daily (n=270) or ARPI (enzalutamide or abiraterone acetate; n=60) or docetaxel (n=75). Randomization was stratified by ECOG performance status (0 or 1), hepatic metastases (present or not), and type of mutation (BRCA1, BRCA2, or ATM). If patients were being treated with androgen deprivation therapy (ADT), therapy was continued throughout the study. Bone-targeted agents were allowed.

Of the 302 patients with BRCAm disease, the median age was 69 years (range: 45 to 92 years); 75% were White, 5% Black, 1.3% Asian, 0.3% American Indian or Alaska Native, 1% multiple races, and 18% unknown; 1.7% were Hispanic/Latino; and baseline ECOG performance status (PS) was 0 (49%) or 1 (51%). Forty percent of patients had bone-only disease; 32% had visceral disease. In the mCSPC setting, 23% of patients had received docetaxel. Among those with BRCAm disease, 40 patients had BRCA1 mutations, and 262 patients had BRCA2 mutations.

The major efficacy outcome measure was radiographic progression-free survival (rPFS) as determined by independent radiology review (IRR) using RECIST version 1.1 and Prostate Cancer Clinical Trials Working Group 3 (PCWG3) (bone) criteria. Additional efficacy outcome measures included overall survival (OS) and IRR-assessed objective response rate (ORR).

TRITON3 demonstrated a statistically significant improvement in IRR-assessed rPFS for RUBRACA compared to ARPI or docetaxel in patients with BRCAm and in the overall population. In an exploratory analysis in the subgroup of 103 (25%) patients with ATMmutations, the rPFS hazard ratio was 0.95 (95% CI: 0.59, 1.52) and the OS hazard ratio was 1.21 (95% CI: 0.77, 1.90), indicating that the improvement in the overall population was primarily attributed to the results seen in the subgroup of patients with BRCAm. Of patients with BRCAm who were randomized to receive ARPI or docetaxel (n=101), 52% crossed over to receive RUBRACA after disease progression.

Efficacy results of the BRCAm population in TRITON3 are provided in Table 9, Figure 2 and Figure 3.

Table 9. Efficacy Results from the BRCAm Subgroup of the TRITON3 Study
Endpoint | Rubraca; N=201f | ARPI or Docetaxel; N=101f
Radiographic Progression Free Survivala
Number of events, n (%) | 115 (57%) | 67 (66%)
Median in months (95% CI) | 11.2 (9.2-13.8) | 6.4 (5.4-8.3)
Hazard ratiob (95% CI) | 0.50 (0.36, 0.69)
p-valuec | < 0.0001
Overall Survivald
Number of events, n (%) | 152 (76%) | 74 (73%)
Median in months (95% CI) | 23.2 (19.1, 25.2) | 21.2 (18.0, 23.1)
Hazard ratiob(95% CI) | 0.91 (0.68, 1.20)
p-valuec | NS
Confirmed Overall Response Ratea,e
 | N=82 | N=41
Overall response rate (95% CI) | 45.1 (34.1, 56.5) | 17.1 (7.2, 32.1)
Number of complete responses, n (%) | 10 (12.2) | 2 (4.9)
Number of partial responses, n (%) | 27 (32.9) | 5 (12.2)
NS=Not significant
aBased on IRR assessment.
bCox proportional hazards model stratified by ECOG Status (0 or 1) and type of mutation (BRCA1 or BRCA2).
cP-value based on the stratified log-rank test
dBased on pre-specified final analysis.
eBased on patients with measurable disease at baseline per IRR assessment. Responses are based on soft tissue and bone lesion assessment.
fBased on the BRCA mutation status used at the randomization. This excludes one patient with a reported ATM mutation at randomization but found to have a BRCA2 mutation based on the verified source.

Figure 2 Kaplan-Meier Curves of rPFS from the BRCAm Subgroup of the TRITON3 Study (IRR-assessed)

Figure 3 Kaplan-Meier Curves of Final OS from the BRCAm Subgroup of the TRITON3 Study

Exploratory subgroup analysis of rPFS and OS for patients with BRCA1m and BRCA2m (including one patient with a BRCA2 mutation mischaracterized as having an ATM mutation at randomization) were performed. The rPFS and OS hazard ratios were 1.01 (95% CI: 0.48, 2.13) and 0.96 (95% CI: 0.46, 2.00) respectively in the subgroup with BRCA1 mutations (n=40) and 0.46 (95% CI: 0.33, 0.65) and 0.92 (95% CI: 0.68, 1.24) respectively in the subgroup with BRCA2 mutations (n=263).

TRITON2

The efficacy of Rubraca was investigated in TRITON2 (NCT02952534), an ongoing multi-center, single arm clinical trial in patients with BRCA-mutated mCRPC who had been treated with androgen receptor-directed therapy and taxane-based chemotherapy. There were 115 patients with either germline or somatic BRCAmutations enrolled in TRITON2, of whom 62 patients had measurable disease at baseline by independent radiology review (IRR). Patients received Rubraca 600 mg orally twice daily until disease progression or unacceptable toxicity. Patients also received concomitant GnRH analog or had prior bilateral orchiectomy. Objective response rate (ORR) and duration of response (DOR) were assessed in patients with measurable disease by blinded IRR and by the investigator according to modified RECIST v1.1/ Prostate Cancer Working Group 3 (PCWG3) criteria.

For the 62 patients with measurable disease at baseline, the median age was 73 years (range 52 to 88); the majority were White (73%) and 10% were Black; and 98% of patients had an ECOG performance status of 0 or 1. All patients had received at least one prior androgen receptor-directed therapy, 34% had received 2 prior androgen receptor-directed therapies and 2% had received 3 prior androgen receptor-directed therapies, and all patients also received prior taxane chemotherapy. Eighteen percent of patients had lung and 21% had liver metastases at baseline. Twenty-four percent had metastases to lymph nodes alone. Forty percent had 10 or more bone lesions at baseline.

All 62 patients had a deleterious somatic or germline BRCAmutation detected from either central plasma (26%), central tissue (32%), or local (42%) testing. Of the 62 patients, 66% had a somatic BRCAmutation, 34% had a germline BRCA mutation, 85% had a BRCA2 mutation, and 15% had a BRCA1 mutation.

The major efficacy outcomes of the study were confirmed ORR by IRR using modified RECIST v1.1/PCWG3 criteria and DOR. Efficacy results of TRITON2 are provided in Table 10. The ORR by IRR was similar in patients with germline versus somatic BRCA mutation.

Table 10. Efficacy Results in Patients with BRCA-mutated mCRPC - TRITON2 (IRR-assessed)
 | Rubraca (N = 62)
Confirmed Objective Response Rate (95% CI)a | 44% (31, 57)
Median DOR in months (95% CI)b | NE (6.4, NE)
NE = not evaluable
aDefined per modified RECIST v1.1 criteria and with no confirmed bone progression per PCWG3.
bThe range for the DOR was 1.7-24+ months. Fifteen of the 27 (56%) patients with a confirmed objective response had a DOR of ≥6 months.

16 HOW SUPPLIED/STORAGE AND HANDLING

How Supplied

Rubraca is available as 200 mg, 250 mg, and 300 mg tablets.

200 mg Tablets:

- Blue, round, and debossed with “C2” on one side
- Supplied in bottles of 60 tablets (NDC:82154-0783-1)

250 mg Tablets:

- White, diamond, and debossed with “C25” on one side
- Supplied in bottles of 60 tablets (NDC:82154-0784-1)

300 mg Tablets:

- Yellow, oval, and debossed with “C3” on one side
- Supplied in bottles of 60 tablets (NDC:82154-0785-1)

Storage

Store at 20°C to 25°C (68°F to 77°F); excursions permitted to 15°C to 30°C (59°F to 86°F) [ see USP Controlled Room Temperature].

17 PATIENT COUNSELING INFORMATION

Advise the patient to read the FDA-approved patient labeling (Patient Information).

MDS/AML: Advise patients to contact their healthcare provider if they experience weakness, feeling tired, fever, weight loss, frequent infections, bruising, bleeding easily, breathlessness, blood in urine or stool, and/or laboratory findings of low blood cell counts, or a need for blood transfusions. These may be signs of hematological toxicity or a more serious uncommon bone marrow problem called ‘myelodysplastic syndrome’ (MDS) or ‘acute myeloid leukemia’ (AML) which have been reported in patients treated with RUBRACA [see Warnings and Precautions (5.1)].

Embryo-Fetal Toxicity: Advise females to inform their healthcare provider if they are pregnant or become pregnant. Inform female patients of the risk to a fetus and potential loss of the pregnancy [see Use in Specific Populations (8.1)]. Advise females of reproductive potential to use effective contraception during treatment and for 6 months after receiving the last dose of RUBRACA. Advise male patients with female partners of reproductive potential or who are pregnant to use effective contraception during treatment and for 3 months after receiving the last dose of RUBRACA. Advise male patients not to donate sperm during therapy and for 3 months following the last dose of RUBRACA [see Warnings and Precautions (5.2) and Use in Specific Populations (8.1, 8.3)].

Photosensitivity: Advise patients to use appropriate sun protection due to the increased susceptibility to sunburn while taking RUBRACA [see Adverse Drug Reactions (6.1)].

Lactation: Advise females not to breastfeed during treatment and for 2 weeks after the last dose of RUBRACA [see Use in Specific Populations (8.2)].

Dosing Instructions: Instruct patients to take RUBRACA orally twice daily with or without food. Doses should be taken approximately 12 hours apart. Advise patients that if a dose of RUBRACA is missed or if the patient vomits after taking a dose of RUBRACA, patients should not take an extra dose, but take the next dose at the regular time [see Dosage and Administration (2.2)].

Manufactured for:
pharmaand GmbH
Taborstrasse 1
1020 Wien
Austria

Distributed by:
Summit SD, LLC
255 Northwest Victoria Drive, Suite A
Lee’s Summit, MO 64086

RUBRACA is a registered trademark of pharma&.

PATIENT INFORMATION
Rubraca® (roo-brah'-kah)
(rucaparib)
tablets

What is the most important information I should know about Rubraca?

Rubraca may cause serious side effects including:
Bone marrow problems called Myelodysplastic Syndrome (MDS) or a type of cancer of the blood called Acute Myeloid Leukemia (AML).Some people who have cancer and who have received previous treatment with chemotherapy or certain other medicines for their cancer have developed MDS or AML during or after treatment with Rubraca. MDS or AML may lead to death. If you develop MDS or AML, your healthcare provider will stop treatment with Rubraca.
Symptoms of low blood cell counts are common during treatment with Rubraca, but can be a sign of serious problems, including MDS or AML. Tell your healthcare provider if you have any of the following symptoms during treatment with Rubraca:

- weakness
- weight loss
- fever

- frequent infections
- blood in urine or stool
- shortness of breath

- feeling very tired
- bruising or bleeding more easily

Your healthcare provider will do blood tests to check your blood cell counts:

- before treatment with Rubraca.
- every month during treatment with Rubraca.
- weekly if you have low blood cell counts for a long time. Your healthcare provider may stop treatment with Rubraca until your blood cell counts improve.

See "What are possible side effects of Rubraca?"for more information about side effects.

What is Rubraca?
Rubraca is a prescription medicine used in adults for:

- the maintenance treatment of ovarian cancer, fallopian tube cancer, or primary peritoneal cancer with a certain type of inherited (germline) or acquired (somatic) abnormal BRCAgene when your cancer has come back and you are in response (complete or partial response) to a platinum-based chemotherapy.
- the treatment of castration-resistant prostate cancer (prostate cancer that no longer responds to medical or surgical treatment that lowers testosterone):
  - that has spread to other parts of the body, and
  - has a certain type of inherited (germline) or acquired (somatic) abnormal BRCAgene, and you have been treated with certain medicines for your cancer.
  Your healthcare provider will perform a test to make sure Rubraca is right for you.

It is not known if Rubraca is safe and effective in children.

Before you take Rubraca, tell your healthcare provider about all of your medical conditions, including if you:

- are pregnant or plan to become pregnant. Rubraca can harm your unborn baby and may cause loss of pregnancy (miscarriage). You should not become pregnant during treatment with Rubraca.
  - If you are able to become pregnant, your healthcare provider may do a pregnancy test before you start treatment with Rubraca.

Females who are able to become pregnant:

- Your healthcare provider may do a pregnancy test before you start treatment with Rubraca
- Use effective birth control (contraception) during treatment with Rubraca and for 6 months after the last dose of Rubraca. Talk to your healthcare provider about birth control methods that may be right for you.
- Tell your healthcare provider right away if you become pregnant or think you might be pregnant during treatment with Rubraca.

Males with female partners who are pregnant or able to become pregnant:

- Use effective birth control (contraception) during treatment with Rubraca and for 3 months after the last dose of Rubraca.
- Do not donate sperm during treatment with Rubraca and for 3 months after the last dose of Rubraca.
- are breastfeeding or plan to breastfeed. It is not known if Rubraca passes into breast milk. Do not breastfeed during treatment and for 2 weeks after the last dose of Rubraca. Talk to your healthcare provider about the best way to feed your baby during this time.

Tell your healthcare provider about all the medicines you take, including prescription and over-the-counter medicines, vitamins, and herbal supplements. Rubraca may affect the way other medicines work.

How should I take Rubraca?

- Take Rubraca exactly as your healthcare provider tells you.
- Your healthcare provider may temporarily stop treatment with Rubraca or change your dose of Rubraca if you have side effects. Do not change your dose or stop taking Rubraca unless your healthcare provider tells you to.
- Take Rubraca 2 times a day. Each dose should be taken about 12 hours apart.
- Take Rubraca with or without food.
- If you are taking Rubraca for prostate cancer and you are receiving gonadotropin-releasing hormone (GnRH) analog therapy, you should continue with this treatment during your treatment with Rubraca unless you have had a surgery to lower the amount of testosterone in your body (surgical castration).
- If you miss a dose of Rubraca, take your next dose at your usual scheduled time. Do not take an extra dose to make up for a missed dose.
- If you vomit after taking a dose of Rubraca, do not take an extra dose. Take your next dose at your usual time.
- If you take too much Rubraca, call your healthcare provider or go to the nearest emergency room right away.

What should I avoid while taking Rubraca?
Avoid spending time in sunlight. Rubraca can make your skin sensitive to the sun (photosensitivity). You may sunburn more easily during treatment with Rubraca. You should wear a hat and clothes that cover your skin and use sunscreen to help protect against sunburn if you have to be in the sunlight.

What are the possible side effects of Rubraca?

Rubraca may cause serious side effects.

- See "What is the most important information I should know about Rubraca?"

The most common side effects of Rubraca in people with ovarian cancer include:

- nausea
- tiredness or weakness
- decrease in hemoglobin (anemia)
- changes in liver and kidney function tests
- vomiting
- diarrhea
- decreased appetite

- low blood cell counts
- changes in how food tastes
- shortness of breath
- dizziness
- indigestion
- reaction to sunlight

The most common side effects of Rubraca in people with prostate cancer include:

- tiredness or weakness
- muscle and joint pain
- nausea
- decrease in hemoglobin (anemia)
- decreased appetite
- changes in liver and kidney function tests
- constipation
- diarrhea
- vomiting
- low blood cell counts
- shortness of breath
- swelling in your legs and feet

- dizziness
- decreased weight
- stomach area (abdominal) pain
- changes in how food tastes
- rash
- tingling sensation and numbness
- urinary tract infection
- cough
- headache
- bleeding
- reaction to sunlight

These are not all of the possible side effects of Rubraca. For more information, ask your healthcare provider or pharmacist.
Call your healthcare provider for medical advice about side effects. You may report side effects to FDA at 1-800-FDA-1088.

How should I store Rubraca?

- Store Rubraca at room temperature between 68°F to 77°F (20°C to 25°C).

Keep Rubraca and all medicines out of the reach of children.

General information about the safe and effective use of Rubraca.
Medicines are sometimes prescribed for purposes other than those listed in a Patient Information leaflet. Do not use Rubraca for a condition for which it was not prescribed. Do not give it to other people, even if they have the same symptoms you have. It may harm them. You can ask your healthcare provider or pharmacist for more information about Rubraca.

What are the ingredients in Rubraca?
Active ingredient:rucaparib
Inactive ingredients:microcrystalline cellulose, sodium starch glycolate, colloidal silicon dioxide, and magnesium stearate. The film coating contains polyvinyl alcohol, titanium dioxide, polyethylene glycol/macrogol, and talc. The blue film coating contains brilliant blue aluminum lake and indigo carmine aluminum lake. The yellow film coating contains yellow iron oxide.

Manufactured for: pharmaand GmbH, Taborstrasse 1, 1020 Wien, Austria

Distributed by: Summit SD LLC, 420 NW Capital Drive, Lee’s Summit, MO 64086

For more information call tel: 1-800-506-8501

This Patient Information has been approved by the U.S. Food and Drug Administration.

Revised: December 2025

PACKAGE LABEL

Principal Display Panel - Rubraca tablets 200 mg Bottle Label

NDC 82154-0783-1

Rubraca®

(rucaparib)tablets

200 mg*

60 tablets

Each tablet contains 344 mg rucaparib camsylate equivalent to 200 mg rucaparib

Rx only

Keep out of reach of children

PACKAGE LABEL

Principal Display Panel - Rubraca tablets 250 mg Bottle Label

NDC 82154-0784-1

Rubraca®

(rucaparib)tablets

250 mg*

60 tablets

Each tablet contains 430 mg rucaparib camsylate equivalent to 250 mg rucaparib

Rx only

Keep out of reach of children

PACKAGE LABEL

Principal Display Panel - Rubraca tablets 300 mg Bottle Label

NDC 82154-0785-1

Rubraca®

(rucaparib)tablets

300 mg*

60 tablets

Each tablet contains 516 mg rucaparib camsylate equivalent to 300 mg rucaparib

Rx only

Keep out of reach of children